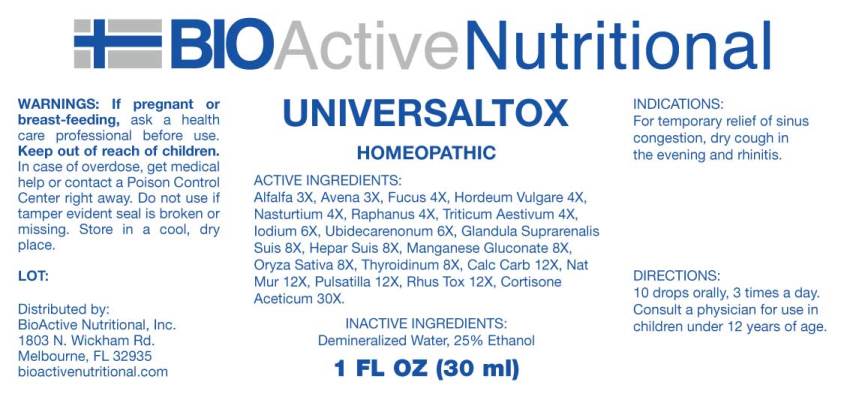 DRUG LABEL: Universaltox
NDC: 43857-0534 | Form: LIQUID
Manufacturer: BioActive Nutritional, Inc.
Category: homeopathic | Type: HUMAN OTC DRUG LABEL
Date: 20241018

ACTIVE INGREDIENTS: ALFALFA 3 [hp_X]/1 mL; AVENA SATIVA FLOWERING TOP 3 [hp_X]/1 mL; FUCUS VESICULOSUS 4 [hp_X]/1 mL; HORDEUM VULGARE TOP 4 [hp_X]/1 mL; NASTURTIUM OFFICINALE 4 [hp_X]/1 mL; DAIKON 4 [hp_X]/1 mL; TRITICUM AESTIVUM WHOLE 4 [hp_X]/1 mL; IODINE 6 [hp_X]/1 mL; UBIDECARENONE 6 [hp_X]/1 mL; SUS SCROFA ADRENAL GLAND 8 [hp_X]/1 mL; PORK LIVER 8 [hp_X]/1 mL; MANGANESE GLUCONATE 8 [hp_X]/1 mL; BROWN RICE 8 [hp_X]/1 mL; THYROID 8 [hp_X]/1 mL; OYSTER SHELL CALCIUM CARBONATE, CRUDE 12 [hp_X]/1 mL; SODIUM CHLORIDE 12 [hp_X]/1 mL; PULSATILLA PRATENSIS WHOLE 12 [hp_X]/1 mL; TOXICODENDRON PUBESCENS LEAF 12 [hp_X]/1 mL; CORTISONE ACETATE 30 [hp_X]/1 mL
INACTIVE INGREDIENTS: WATER; ALCOHOL

DRUG FACTS:

ACTIVE INGREDIENTS:

Alfalfa 3X, Avena Sativa 3X, Fucus Vesiculosus 4X, Hordeum Vulgare 4X, Nasturtium Aquaticum 4X, Raphanus Sativus 4X, Triticum Aestivum 4X, Iodium 6X, Ubiquinone 6X, Glandula Suprarenalis Suis 8X, Hepar Suis 8X, Manganum Gluconate 8X, Oryza Sativa 8X, Thyroidinum (Suis) 8X, Calcarea Carbonica 12X, Natrum Muriaticum 12X, Pulsatilla (Pratensis) 12X, Rhus Tox 12X, Cortisone Aceticum 30X.

INDICATIONS:

For temporary relief of sinus congestion, dry cough in the evening and rhinitis.

WARNINGS:

If pregnant or breast-feeding, ask a health care professional before use.

Keep out of reach of children. In case of overdose, get medical help or contact a Poison Control Center right away.

Do not use if tamper evident seal is broken or missing.

Store in a cool, dry place.

Keep out of reach of children. In case of overdose, get medical help or contact a Poison Control Center right away.

DIRECTIONS:

10 drops orally, 3 times a day. Consult a physician for use in children under 12 years of age.

INDICATIONS:

For temporary relief of sinus congestion, dry cough in the evening and rhinitis.

INACTIVE INGREDIENTS:

Demineralized water, 25% Ethanol.

QUESTIONS:

Distributed by:

BioActive Nutritional, Inc.

1803 N. Wickham Rd.

Melbourne, FL 32935

bioactivenutritional.com

PACKAGE DISPLAY LABEL:

BIOActive Nutritional

UNIVERSALTOX

HOMEOPATHIC

1 FL OZ (30 ml)